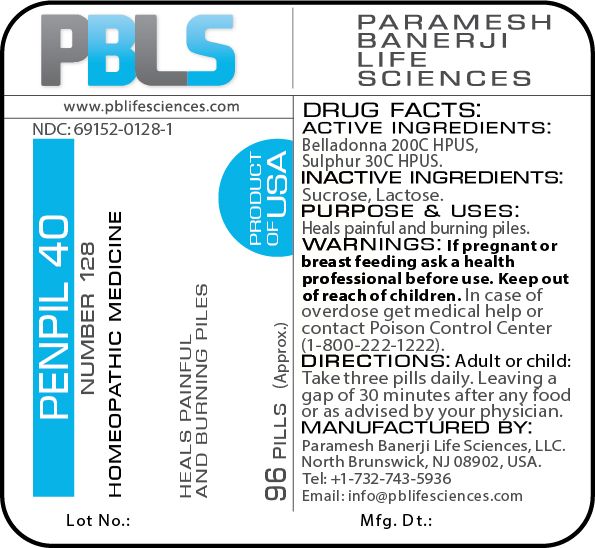 DRUG LABEL: Penpil 40 (Number 128)
NDC: 69152-0128 | Form: PELLET
Manufacturer: Paramesh Banerji Life Sciences LLC
Category: homeopathic | Type: HUMAN OTC DRUG LABEL
Date: 20180725

ACTIVE INGREDIENTS: SULFUR 30 [hp_C]/1 1; ATROPA BELLADONNA 200 [hp_C]/1 1
INACTIVE INGREDIENTS: SUCROSE; LACTOSE

DRUG FACTS: Active Ingredients

Belladonna 200C HPUS, Sulphur 30C HPUS

Inactive Ingredients

Sucrose, Lactose

Purpose

Heals painful and burning piles

Uses

Heals painful and burning piles

Warnings

If pregnant or breast feeding ask a health professional before use.

Keep out of reach of children. In case of overdose, get medical help or contact a Poison Control Center (1-800-222-1222) right away.

Direction

Adult or child: Take three pills daily. Leaving a gap of 30 minutes after any food or as advised by your physician.

Manufactured by

Paramesh Banerji Life Sciences, LLC.

North Brunswick, NJ 08902, USA.

Tel: +1-732-743-5936

Email: info@pblifesciences.com

Principal Display Panel

NDC: 69152-0128-1

Penpil 40

Number 128

Homeopathic Medicine

Heals painful and burning piles

96 Pills (Approx.)

Product of USA